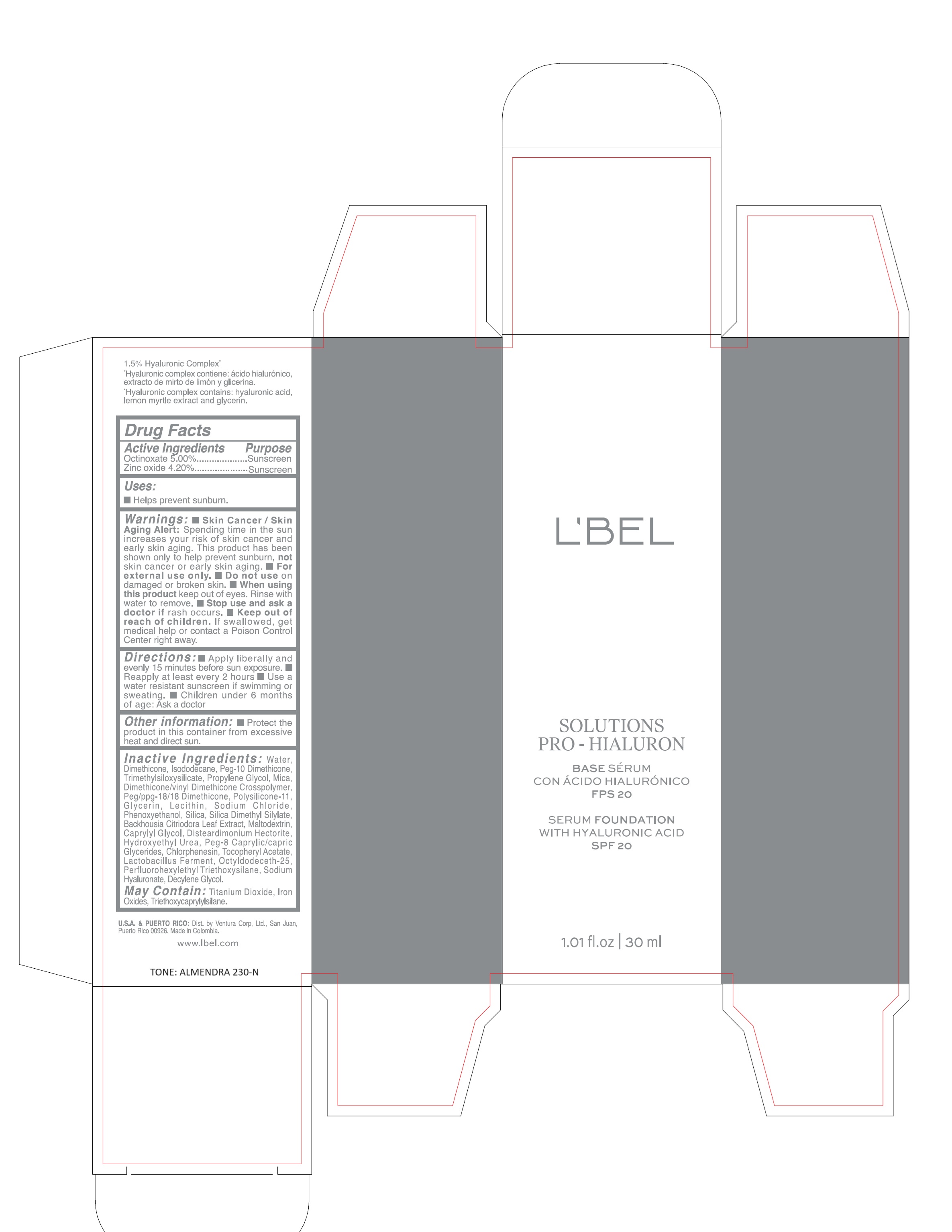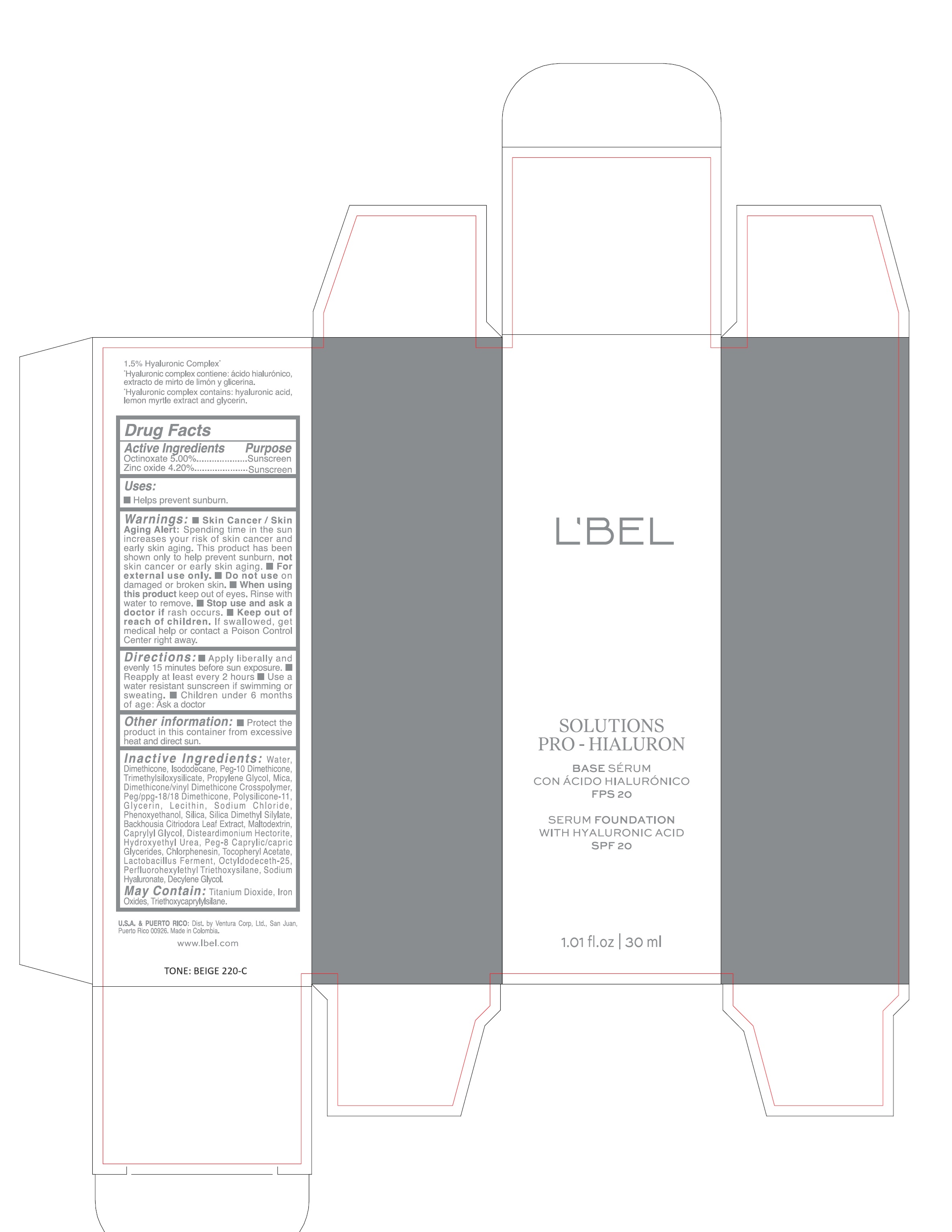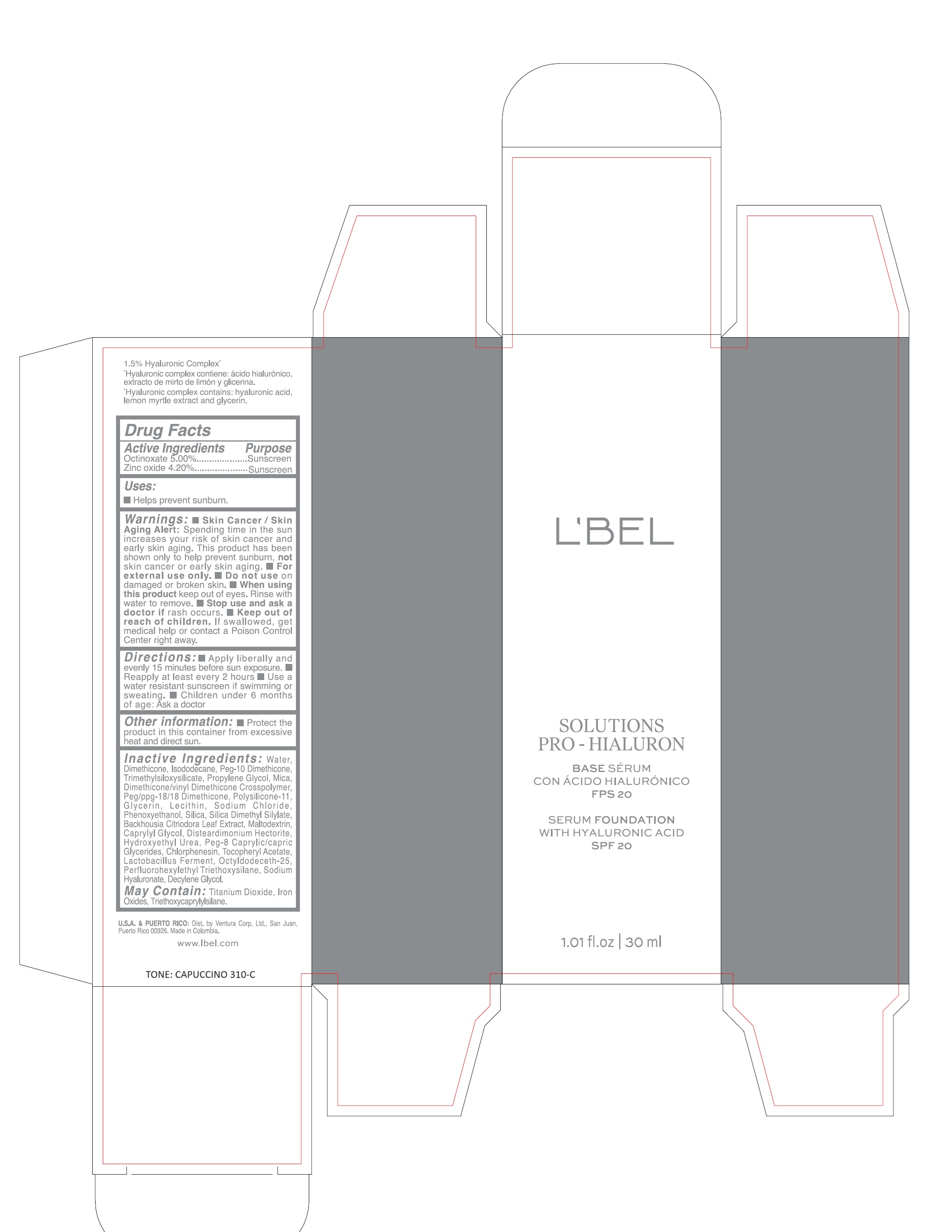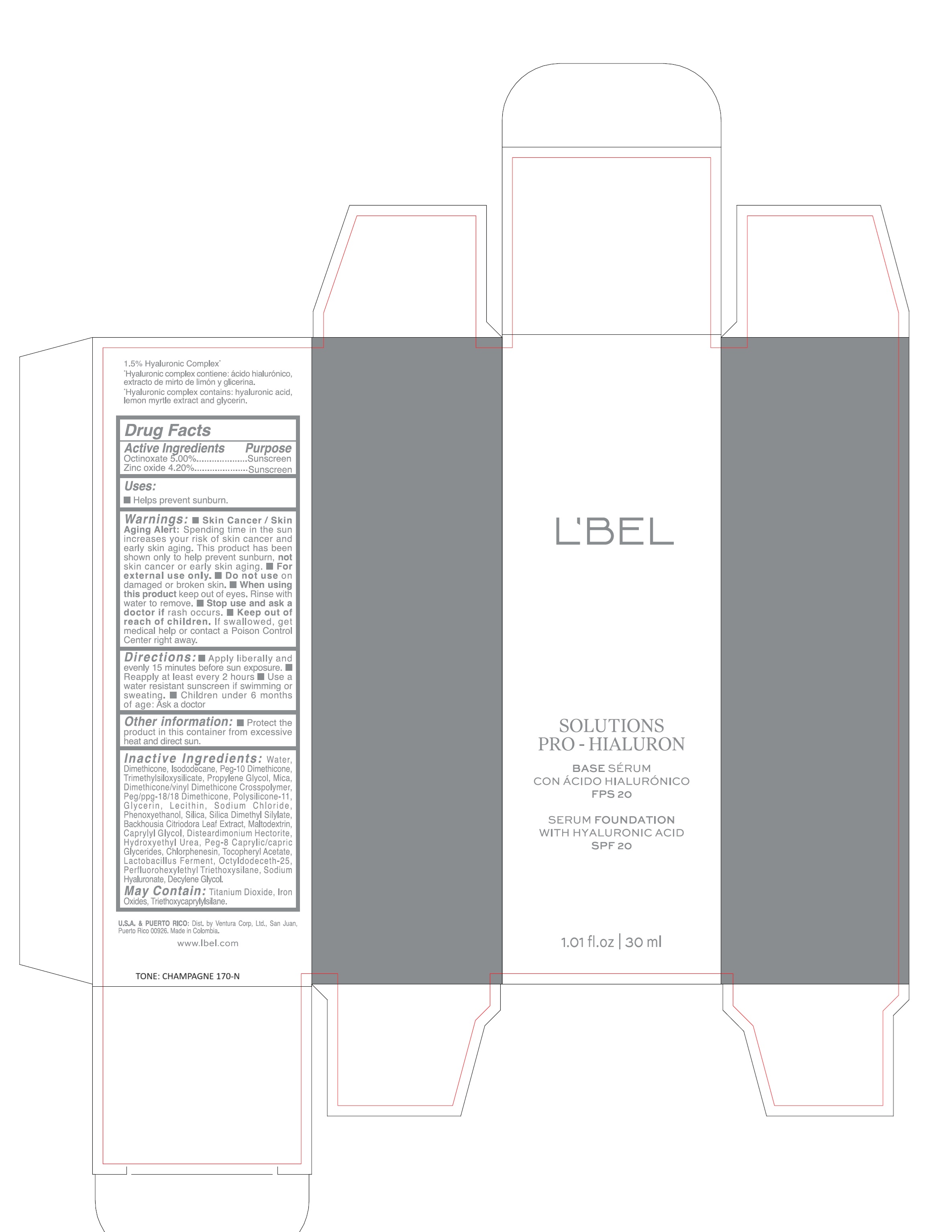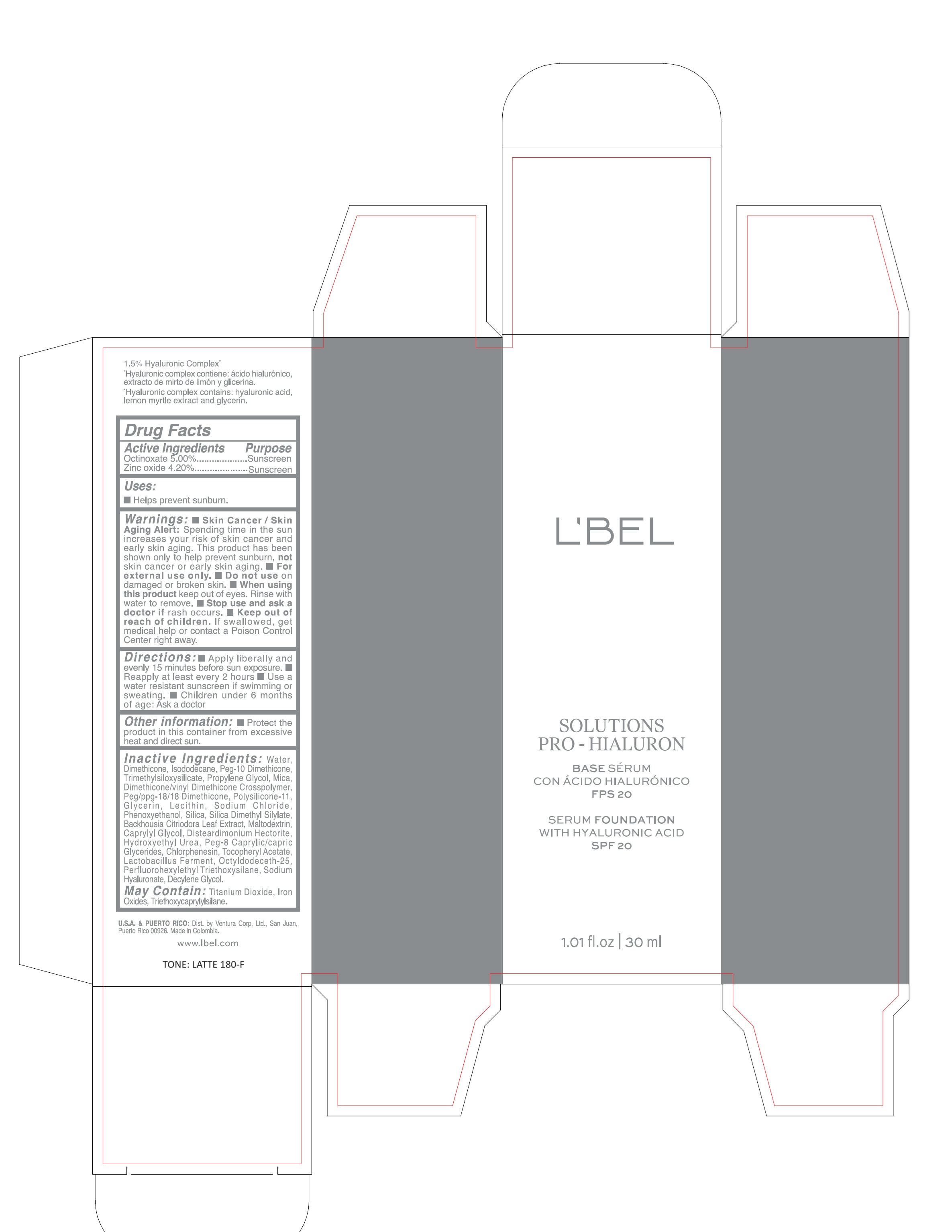 DRUG LABEL: LBEL SOLUTIONS PRO-HIALURON BASE SERUM CON ACIDO HIALURONICO FPS 20 SERUM FOUNDATION WITH HYALURONIC ACID SPF 20 CHAMPAGNE 170-N
NDC: 14141-321 | Form: EMULSION
Manufacturer: BEL STAR SA
Category: otc | Type: HUMAN OTC DRUG LABEL
Date: 20250622

ACTIVE INGREDIENTS: OCTINOXATE 50 mg/1 mL; ZINC OXIDE 42 mg/1 mL
INACTIVE INGREDIENTS: WATER; TITANIUM DIOXIDE; SILICON DIOXIDE; SILICA DIMETHYL SILYLATE; DIMETHICONE/VINYL DIMETHICONE CROSSPOLYMER (SOFT PARTICLE); DIMETHICONE/VINYL DIMETHICONE CROSSPOLYMER (HARD PARTICLE); LECITHIN, SOYBEAN; BACKHOUSIA CITRIODORA LEAF; PEG-8 CAPRYLIC/CAPRIC GLYCERIDES; PERFLUOROOCTYL TRIETHOXYSILANE; SODIUM CHLORIDE; DISTEARDIMONIUM HECTORITE; PHENOXYETHANOL; HYDROXYETHYL UREA; CHLORPHENESIN; LIMOSILACTOBACILLUS FERMENTUM; FERRIC OXIDE YELLOW; TRIETHOXYCAPRYLYLSILANE; FERRIC OXIDE RED; GLYCERIN; OCTYLDODECETH-25; MALTODEXTRIN; DECYLENE GLYCOL; FERROSOFERRIC OXIDE; DIMETHICONE; PEG-10 DIMETHICONE (220 CST); ISODODECANE; TRIMETHYLSILOXYSILICATE (M/Q 0.8-1.0); PROPYLENE GLYCOL; MICA; PEG/PPG-18/18 DIMETHICONE; CAPRYLYL GLYCOL; ALPHA-TOCOPHEROL ACETATE; HYALURONATE SODIUM

LBEL SOLUTIONS PRO-HIALURON BASE SERUM CON ACIDO HIALURONICO FPS 20
SERUM FOUNDATION WITH HYALURONIC ACID SPF 20

Active ingredients

Octinoxate 5.00%

Zinc oxide 4.20%

Purpose

Sunscreen

Uses

- Helps prevent sunburn.

Warnings

- Skin Cancer/Skin Aging Alert: Spending time in the sun increases your risk of skin cancer and early skin aging. This product has been shown only to help prevent sunburn, not skin cancer or early skin aging.
- For external use only.

Do not use

on damaged or broken skin.

When using this product

keep out of eyes. Rinse with water to remove.

Stop use and ask a doctor if

rash occurs.

Keep out of reach of children.

If swallowed, get medical help or contact a Poison Control Center right away.

Directions

- Apply liberally and evenly 15 minutes before sun exposure.
- Reapply at least every 2 hours.
- Use a water resistant sunscreen if swimming or sweating.
- Children under 6 months of age: Ask a doctor

Other information

Protect the product in this container from excessive heat and direct sun.

Inactive ingredients

Water, Dimethicone, Isododecane, Peg-10 Dimethicone, Trimethylsiloxysilicate, Propylene Glycol, Mica, Dimethicone/vinyl Dimethicone Crosspolymer, Peg/ppg-18/18 Dimethicone, Polysilicone-11, Glycerin, Lecithin, Sodium Chloride, Phenoxyethanol, Silica, Silica Dimethyl Silylate, Backhousia Citriodora Leaf Extract, Maltodextrin, Caprylyl Glycol, Disteardimonium Hectorite, Hydroxyethyl Urea, Peg-8 Caprylic/capric Glycerides, Chlorphenesin, Tocopheryl Acetate, Lactobacillus Ferment, Octyldodeceth-25, Perfluorohexylethyl Triethoxysilane, Sodium Hyaluronate, Decylene Glycol.

May Contain: Titanium Dioxide, Iron Oxides, Triethoxycaprylylsilane.

Company Information

U.S.A. & PUERTO RICO: Dist. by Ventura Corp, Ltd., San Juan, Puerto Rico 00926, Made in Colombia.

www.lbel.com